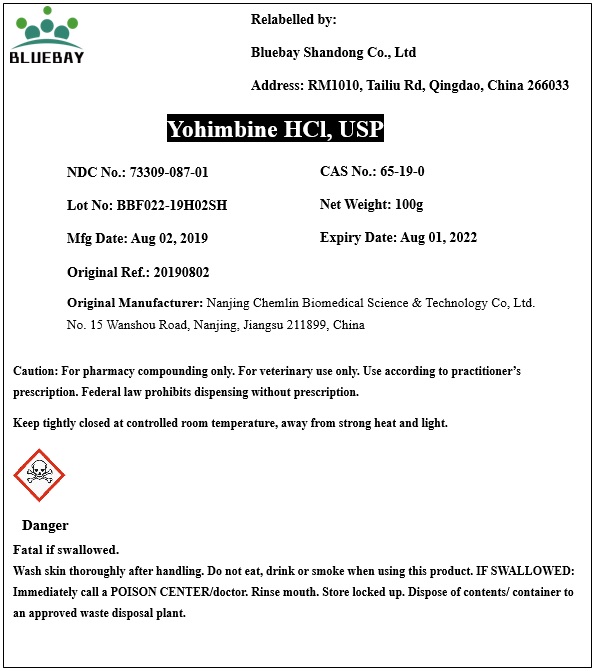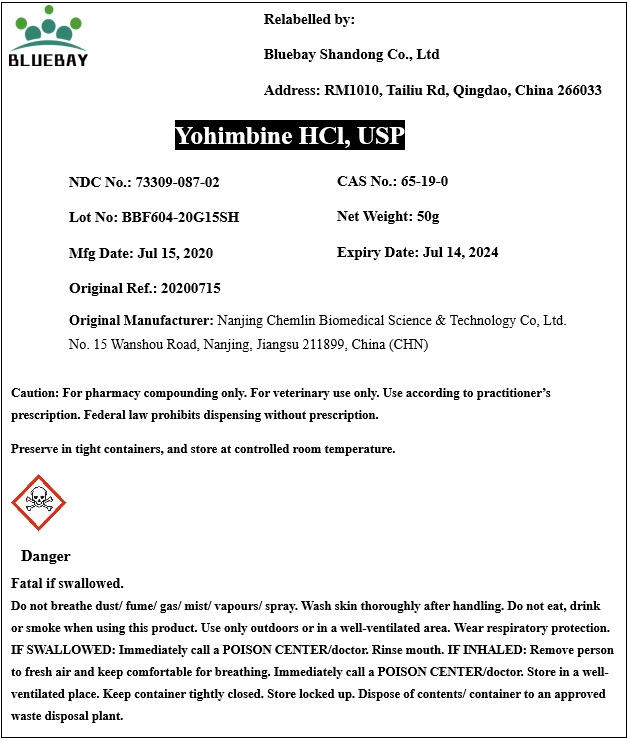 DRUG LABEL: Yohimbine HCl
NDC: 73309-087 | Form: POWDER
Manufacturer: BLUEBAY SHANDONG CO.,LTD
Category: other | Type: BULK INGREDIENT
Date: 20201218

ACTIVE INGREDIENTS: YOHIMBINE HYDROCHLORIDE 1 g/1 g

Yohimbine HCl